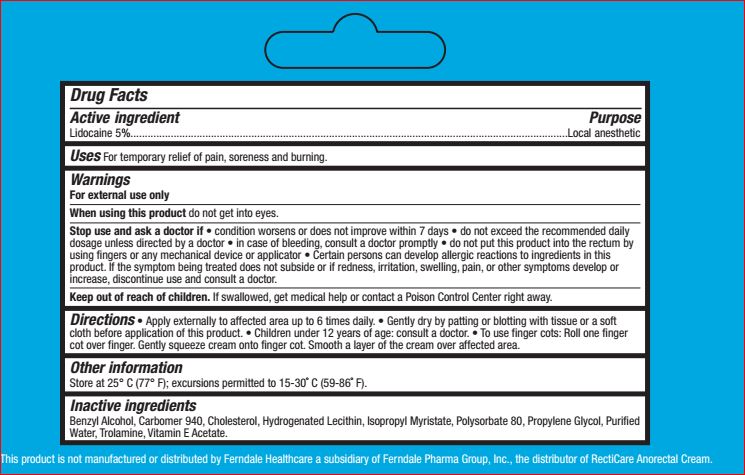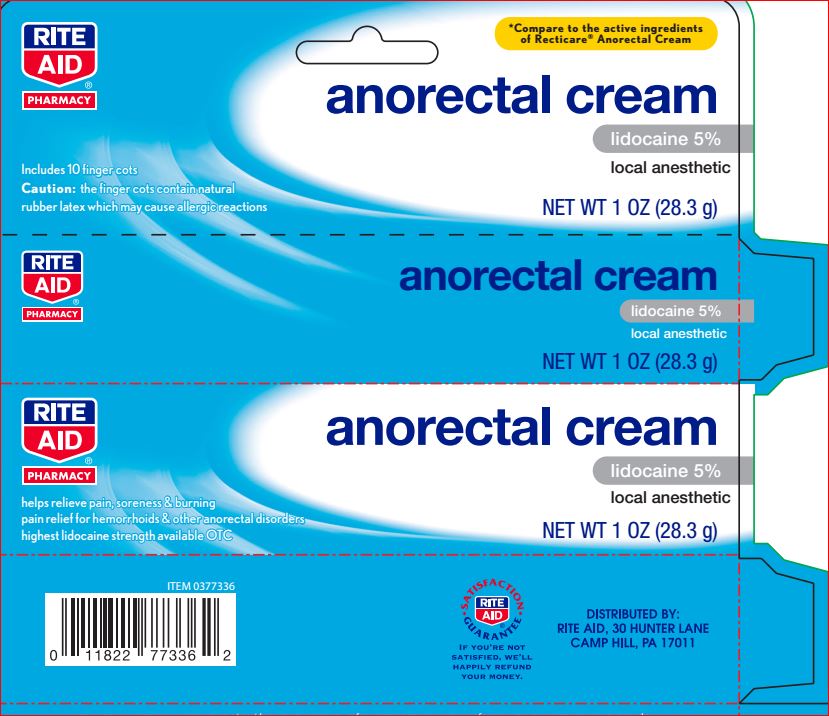 DRUG LABEL: Anorectal
NDC: 11822-1234 | Form: CREAM
Manufacturer: Rite Aid
Category: otc | Type: HUMAN OTC DRUG LABEL
Date: 20180618

ACTIVE INGREDIENTS: Lidocaine 5 g/100 mL
INACTIVE INGREDIENTS: Benzyl alcohol; Cholesterol; HYDROGENATED SOYBEAN LECITHIN; Isopropyl Myristate; Polysorbate 80; Propylene Glycol; Water; Trolamine; .ALPHA.-TOCOPHEROL ACETATE

Drug Facts

Active ingredient Purpose

Lidocaine 5%......................................Local anesthetic

INDICATIONS AND USAGE

Uses For temporary relief of pain, soreness and burning.

Warnings For external use only

When using this product do not get into eyes.
Stop use and ask a doctor if • condition worsens or does
not improve within 7 days • do not exceed the
recommended daily dosage unless directed by a doctor
• in case of bleeding, consult a doctor promptly • do not
put this product into the rectum by using fingers or any
mechanical device or applicator

Certain persons can develop allergic reactions to ingredients in this
product. If the symptom being treated does not subside or if redness, irritation, swelling, pain, or other symptoms develop or
increase, discontinue use and consult a doctor

Keep out of reach of children. If swallowed, get medical help or contact a Poison Control Center right away.

DOSAGE AND ADMINISTRATION

Directions • Apply externally to affected area up to 6 times daily. • Gently dry by patting or blotting with tissue or a soft
cloth before application of this product. • Children under 12 years of age: consult a doctor. • To use finger cots: Roll one finger
cot over finger. Gently squeeze cream onto finger cot. Smooth a layer of the cream over affected area.

Other information Store at 25° C (77° F);
excursions permitted to 15-30˚ C (59-86˚ F).

Inactive ingredients
Benzyl Alcohol, Carbomer 940, Cholesterol, Hydrogenated Lecithin, Isopropyl Myristate, Polysorbate 80, Propylene Glycol, Purified Water, Trolamine, Vitamin E Acetate.